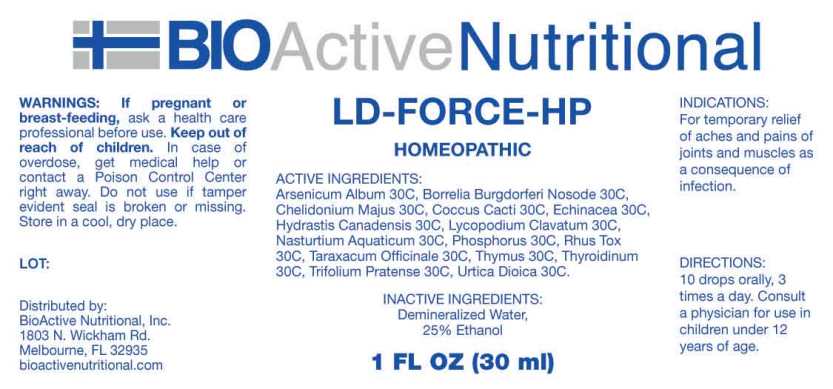 DRUG LABEL: LD Force HP
NDC: 43857-0618 | Form: LIQUID
Manufacturer: BioActive Nutritional, Inc.
Category: homeopathic | Type: HUMAN OTC DRUG LABEL
Date: 20241017

ACTIVE INGREDIENTS: ARSENIC TRIOXIDE 30 [hp_C]/1 mL; BORRELIA BURGDORFERI 30 [hp_C]/1 mL; CHELIDONIUM MAJUS WHOLE 30 [hp_C]/1 mL; PROTORTONIA CACTI 30 [hp_C]/1 mL; ECHINACEA ANGUSTIFOLIA WHOLE 30 [hp_C]/1 mL; GOLDENSEAL 30 [hp_C]/1 mL; LYCOPODIUM CLAVATUM SPORE 30 [hp_C]/1 mL; NASTURTIUM OFFICINALE 30 [hp_C]/1 mL; PHOSPHORUS 30 [hp_C]/1 mL; TOXICODENDRON PUBESCENS LEAF 30 [hp_C]/1 mL; TARAXACUM OFFICINALE 30 [hp_C]/1 mL; SUS SCROFA THYMUS 30 [hp_C]/1 mL; THYROID 30 [hp_C]/1 mL; TRIFOLIUM PRATENSE FLOWER 30 [hp_C]/1 mL; URTICA DIOICA WHOLE 30 [hp_C]/1 mL
INACTIVE INGREDIENTS: WATER; ALCOHOL

DRUG FACTS:

ACTIVE INGREDIENTS:

Arsenicum Album 30C, Borrelia Burgdorferi Nosode 30C, Chelidonium Majus 30C, Coccus Cacti 30C, Echinacea (Angustifolia) 30C, Hydrastis Canadensis 30C, Lycopodium Clavatum 30C, Nasturtium Aquaticum 30C, Phosphorus 30C, Rhus Tox 30C, Taraxacum Officinale 30C, Thymus (Suis) 30C, Thyroidinum (Suis) 30C, Trifolium Pratense 30C, Urtica Dioica 30C.

INDICATIONS:

For temporary relief of aches and pains of joints and muscles as a consequence of infection.

WARNINGS:

If pregnant or breast-feeding, ask a health care professional before use.

Keep out of reach of children. In case of overdose, get medical help or contact a Poison Control Center right away.

Do not use if tamper evident seal is broken or missing.

Store in cool, dry place.

Keep out of reach of children. In case of overdose, get medical help or contact a Poison Control Center right away.

DIRECTIONS:

10 drops orally, 3 times a day. Consult a physician for use in children under 12 years of age.

INDICATIONS:

For temporary relief of aches and pains of joints and muscles as a consequence of infection.

INACTIVE INGREDIENTS:

Demineralized water, 25% Ethanol.

QUESTIONS:

Distributed by:
BioActive Nutritional, Inc.
1803 N. Wickham Rd.
Melbourne, FL 32935
bioactivenutritional.com

PACKAGE LABEL DISPLAY:

BIOActive Nutritional

LD-FORCE HP

HOMEOPATHIC

1 FL OZ (30 ml)